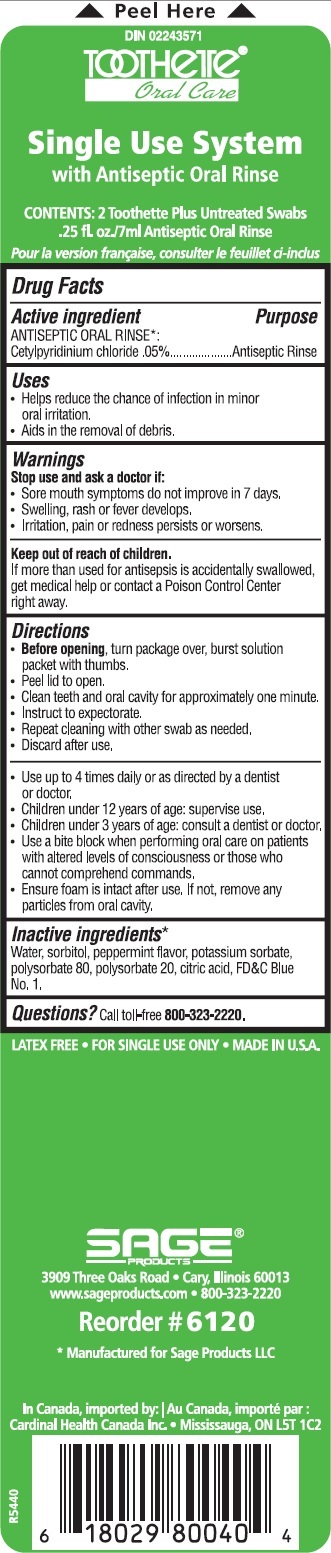 DRUG LABEL: Toothette Oral Care Single Use System with Antiseptic Oral Rinse
NDC: 53462-120 | Form: KIT | Route: BUCCAL
Manufacturer: Sage Products LLC
Category: otc | Type: HUMAN OTC DRUG LABEL
Date: 20140519

ACTIVE INGREDIENTS: CETYLPYRIDINIUM CHLORIDE .5 [iU]/1 mL
INACTIVE INGREDIENTS: SORBITOL; PEPPERMINT; POTASSIUM SORBATE; POLYSORBATE 80; POLYSORBATE 20; CITRIC ACID MONOHYDRATE; FD&C BLUE NO. 1; WATER

Toothette Oral Care Single Use System

Drug Facts

Active ingredient: ANTISEPTIC ORAL RINSE*: | Purpose
Cetylpyridinium chloride .05% | Antiseptic Rinse

Uses

- Helps reduce the chance of infection in minor oral irritation.
- Aids in the removal of debris.

Warnings

Stop use and ask a doctor if:
- Sore mouth symptoms do not improve in 7 days.
- Swelling, rash or fever develops.
- Irritation, pain or redness persists or worsens.

Keep out of reach of children.
If more than used for antisepsis is accidentally swallowed, get medical help or contact a Poison Control Center right away.

Directions

- Before opening, turn package over, burst solution packet with thumbs.
- Peel lid to open.
- Clean teeth and oral cavity for approximately one minute.
- Instruct to expectorate.
- Repeat cleaning with other swab as needed.
- Discard after use.

- Use up to 4 times daily or as directed by a dentist or doctor.
- Children under 12 years of age: supervise use.
- Children under 3 years of age: consult a dentist or doctor.
- Use a bite block when performing oral care on patients with altered levels of consciousness or those who cannot comprehend commands.
- Ensure foam is intact after use. If not, remove any particles from oral cavity.

Inactive ingredients*

Water, sorbitol, peppermint flavor, potassium sorbate, polysorbate 80, polysorbate 20, citric acid, FD&C Blue No. 1.

Questions?

Call toll-free 800-323-2220.

LATEX FREE • FOR SINGLE USE ONLY • MADE IN U.S.A.

* Manufactured for Sage Products LLC

PACKAGE LABEL

Toothette Oral Care Single Use System with Antiseptic Oral Rinse

NDC 53462-120-60